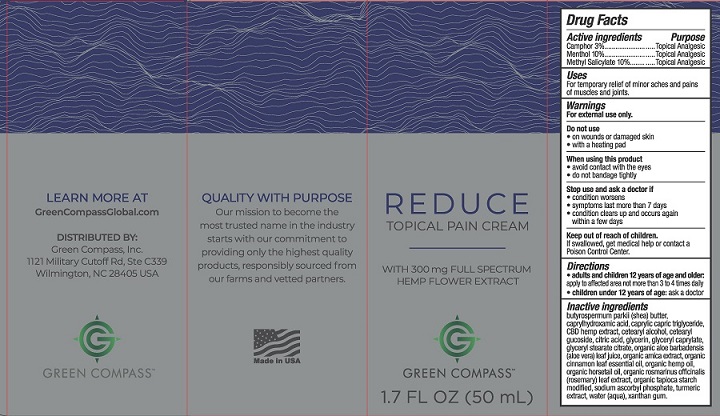 DRUG LABEL: Green Compass Reduce Topical Pain
NDC: 73132-001 | Form: CREAM
Manufacturer: Green Compass, Inc.
Category: otc | Type: HUMAN OTC DRUG LABEL
Date: 20250101

ACTIVE INGREDIENTS: CAMPHOR (NATURAL) 3 g/100 mL; MENTHOL, UNSPECIFIED FORM 10 g/100 mL; METHYL SALICYLATE 10 g/100 mL
INACTIVE INGREDIENTS: XANTHAN GUM; ARNICA MONTANA; CANNABIS SATIVA SEED OIL; GLYCERYL STEARATE CITRATE; CINNAMON LEAF OIL; EQUISETUM ARVENSE WHOLE; TURMERIC; MEDIUM-CHAIN TRIGLYCERIDES; HEMP; CETOSTEARYL ALCOHOL; CETEARYL GLUCOSIDE; CITRIC ACID MONOHYDRATE; GLYCERIN; GLYCERYL CAPRYLATE; SHEA BUTTER; CAPRYLHYDROXAMIC ACID; ALOE VERA LEAF; ROSEMARY; STARCH, TAPIOCA; SODIUM ASCORBYL PHOSPHATE; WATER

Green Compass Reduce Topical Pain Cream

Drug Facts

Active ingredients

Camphor 3%

Menthol 10%

Methyl Salicylate 10%

Purpose

Topical Analgesic

Topical Analgesic

Topical Analgesic

Uses

For temporary relief of minor aches and pains of muscles and joints.

Warnings

For external use only.

Do not use

- on wounds or damaged skin
- with a heating pad

When using this product

- avoid contact with the eyes
- do not bandage tightly

Stop use and ask a doctor if

- condition worsens
- symptoms last more than 7 days
- condition clears up and occurs again within a few days

Keep out of reach of children. If swallowed, get medical help or contact a Poison Control Center right away.

Directions

- adults and children 12 years of age and older: apply to affected area not more than 3 to 4 times daily
- children under 12 years of age: ask a doctor

Inactive ingredients

butyrospermum parkii (shea) butter, caprylhydroxamid acid, caprylic capric triglyceride, CBD hemp extract, cetearyl alcohol, cetearyl glucoside, citric acid, glycerin, glyceryl caprylate, glyceryl stearate citrate, organic aloe barbadensis (aloe vera) leaf juice, organic arnica extract, organic cinnamon leaf essential oil, organic hemp oil, organic horsetail oil, organic rosmarinum officinalis (rosemary) leaf extract, organic tapioca starch modified, sodium ascorbyl phosphate, turmeric extract, water (aqua), xanthan gum.

LEARN MORE AT

GreenCompassGlobal.com

DISTRIBUTED BY:

Green Compass, Inc.

1121 Military Cutoff Rd., Ste C339

Wilmington, NC 28405 USA

PACKAGE LABEL

REDUCE

TOPICAL PAIN CREAM

WITH 300 mg FULL SPECTRUM HEMP FLOWER EXTRACT

GREEN COMPASS

1.7 FL OZ (50 mL)